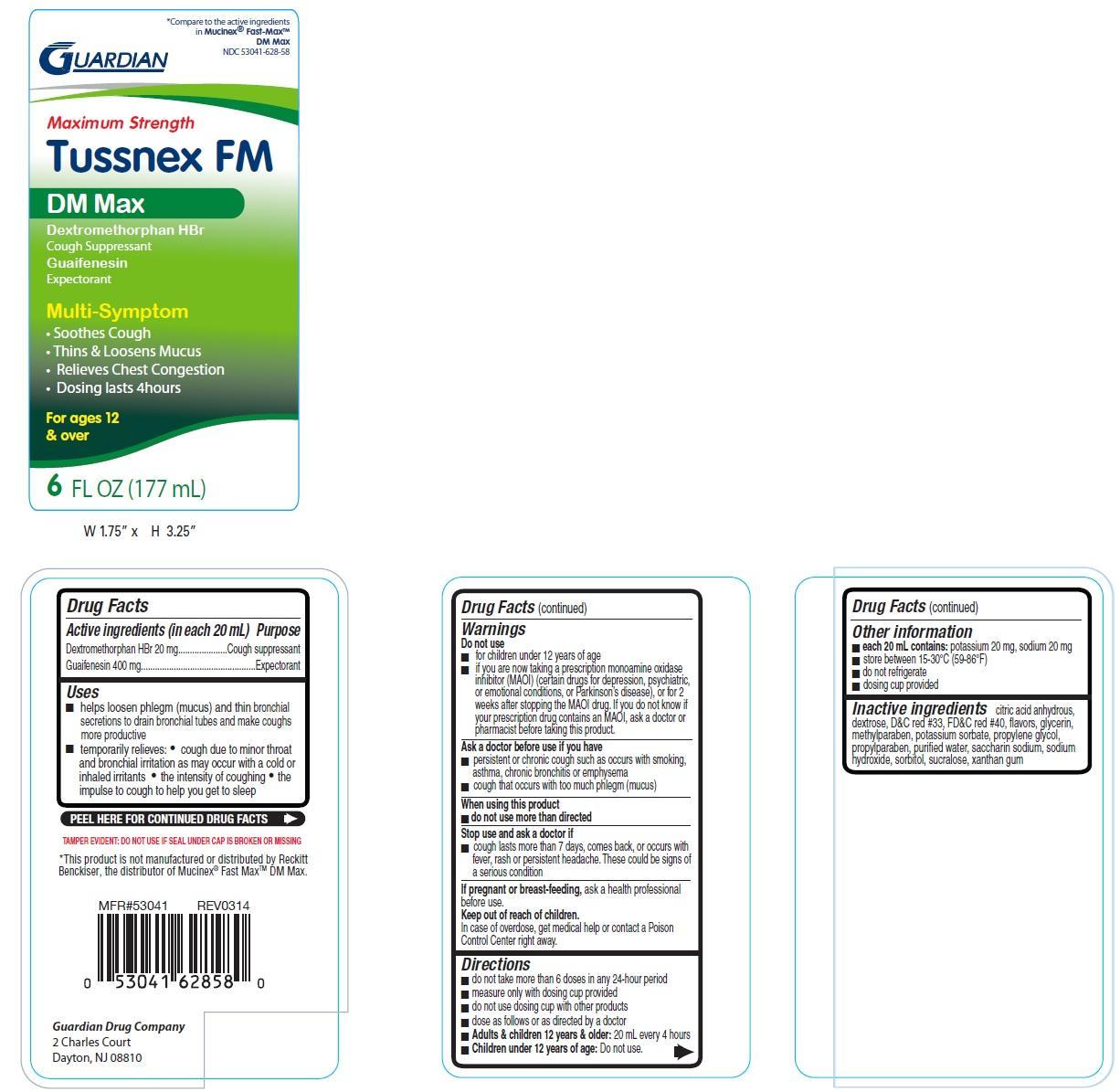 DRUG LABEL: Maximum strength Tussnex FM DM Max
NDC: 53041-628 | Form: LIQUID
Manufacturer: Guardian Drug Company
Category: otc | Type: HUMAN OTC DRUG LABEL
Date: 20241219

ACTIVE INGREDIENTS: DEXTROMETHORPHAN HYDROBROMIDE 20 mg/20 mL; GUAIFENESIN 400 mg/20 mL
INACTIVE INGREDIENTS: ANHYDROUS CITRIC ACID; DEXTROSE; D&C RED NO. 33; FD&C RED NO. 40; GLYCERIN; METHYLPARABEN; POTASSIUM SORBATE; PROPYLENE GLYCOL; PROPYLPARABEN; WATER; SACCHARIN SODIUM; SODIUM HYDROXIDE; SORBITOL; SUCRALOSE; XANTHAN GUM

Tussnex FM DM Max

Active ingredients (in each 20 mL)

Dextromethorphan HBr 20 mg

Guaifenesin 400 mg

Purpose

Cough suppressant

Expectorant

Uses

- helps loosen phlegm (mucus) and thin bronchial secretions to drain bronchial tubes and make coughs more productive
- temporarily relieves:
- cough due to minor throat and bronchial irritation as may occur with a cold or inhaled irritants
- the intensity of coughing
- the impulse to cough to help you get to sleep

Warnings

Do not use

- for children under 12 years of age
- if you are now taking a prescription monoamine oxidase inhibitor (MAOI)(certain drugs for depression, psychiatric, or emotional conditions, or Parkinson's disease), or for 2 weeks after stopping the MAOI drug. If you do not know if your prescription drug contains an MAOI, ask a doctor or pharmacist before taking this product.

Ask a doctor before use if you have

- persistent or chronic cough such as occurs with smoking, asthma, chronuc bronchitis or emphysema
- cough that occurs with too much phlegm (mucus)

When using this product

- do not use more than directed

Stop use and ask a doctor if

- cough lasts more than 7 days, comes back, or occurs with fever, rash or persistent headache. These could be signs of a serious condition.

If pregnant or breast-feeding,

ask a health professional before use.

keep out of reach of children. In case of overdose, get medical help or contact a poison control center right away.

Directions

- do not take more than 6 doses in any 24 hour period
- measure only with dosing cup provided
- do not use dosing cup with other products
- dose as follows or as directed by a doctor
- Adults & children 12 years & older: 20mL every 4 hours
- Children under 12 years of age: Do not use

Other information

- each 20 mL contains: potassium 20 mg, sodium 20 mg
- store between 15-30oC (59-86oF)
- do not refrigerate
- dosing cup provided

Inactive ingredients

citric acid anhydrous, D&C red 33, dextrose, FD&C red 40, flavors, glycerin, methylparaben, potassium sorbate, propylene glycol, propylparaben, purified water, saccharin sodium, sodium hydroxide, sorbitol, sucralose, xanthan gum

PDP

compare to active ingredients in Mucinex®Fast-MaxTMDM Max

Maximum strength

Tussnex FM DM Max

Dextromethorphan HBr

Cough suppressant

Guaifenesin

Expectorant

Multi-symptom

Relieves chest congestion

Thins and loosens mucus

Soothes cough

Dosing lasts 4 hours

For ages 12 & over